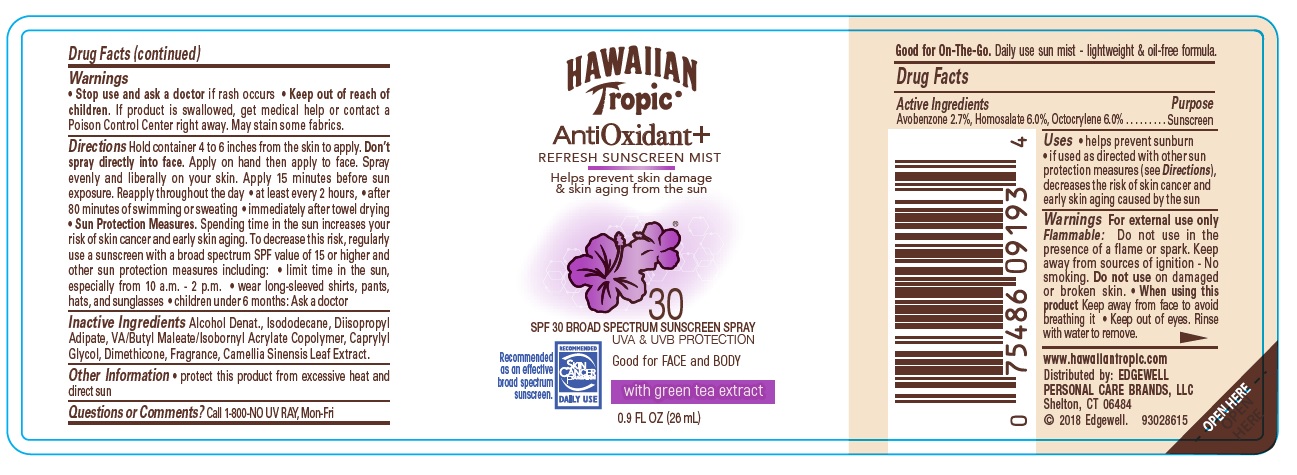 DRUG LABEL: Hawaiian Tropic
NDC: 63354-832 | Form: SPRAY
Manufacturer: Edgewell Personal Care Brands LLC
Category: otc | Type: HUMAN OTC DRUG LABEL
Date: 20250822

ACTIVE INGREDIENTS: HOMOSALATE 6 g/100 g; AVOBENZONE 2.7 g/100 g; OCTOCRYLENE 6 g/100 g
INACTIVE INGREDIENTS: CAPRYLYL GLYCOL; DIMETHICONE; CAMELLIA SINENSIS WHOLE; ALCOHOL; ISODODECANE; DIISOPROPYL ADIPATE

Active Ingredient

Avobenzone 2.7%, Homosalate 6.0%, Octocrylene 6.0%

Purpose

Sunscreen

Uses

Helps prevent sunburn.

If used as directed with other sun protection measures (see Directions), decreases the risk of skin cancer and early skin aging caused by the sun.

Warnings

For external use only

Flammable

Do not use in the presence of a flame or spark. Keep away from sources of ignition - No smoking.

Do not use

on damaged or broken skin

When using this product

Keep away from face to avoid breathing it. Keep out of eyes. Rinse with water to remove.

Stop use and ask a doctor

if rash occurs.

Keep out of reach of children

If product is swallowed, get medical help or contact a Poison Control Center right away.

May stain

some fabrics.

Directions

Hold container 4 to 8 inches from the skin to apply. Don't spray directly into face. Apply on hand then apply to face. Spray evenly and liberatly on your skin. Apply 15 minutes before sun exposure. Reapply throughout the day. • at least every 2 hours • after 80 minutes of swimming or sweating • immediately after towel drying • Sun Protection Measures. Spending time in the sun increases your risk of skin cancer and early skin aging. To decrease this risk, regularly use a sunscreen with a broad spectrum SPF value of 15 or higher and other sun protection measures including: • limit time in the sun, especially from 10 a.m. - 2 p.m. • wear long-sleeved shirts,pants, hats, and sunglasses • Children under 6 months: Ask a doctor.

Inactive Ingredients

Alcohol Denat., Isododecane, Diisopropyl Adipate, VA/Butyl Maleate/Isobornyl Acrylate Copolymer, Caprylyl Glycol, Dimethicone, Fragrance, Camellia Sinensis Leaf Extract.

Other Information

Protect this product from excessive heat and direct sun.

Questions or Comments?

Call 1-800-NO UV RAY, Mon-Fri

PACKAGE LABEL

HAWAIIAN

Tropic

AntiOxidant+

REFRESH SUNSCREEN MIST

Helps prevent skin damage

& skin aging from the sun

30

SPF 30 BROAD SPECTRUM SUNSCREEN SPRAY

UVA & UVB PROTECTION

Good for FACE and BODY

with green tea extract.